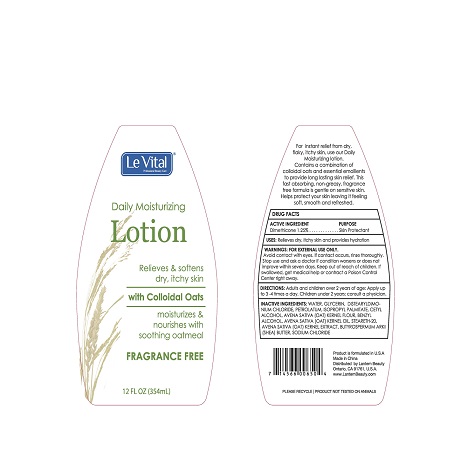 DRUG LABEL: Daily Moisturizing with Colloidal Oats
NDC: 50306-010 | Form: LOTION
Manufacturer: Shanghai Lantern Cosmetic Co
Category: otc | Type: HUMAN OTC DRUG LABEL
Date: 20160516

ACTIVE INGREDIENTS: CETYL ALCOHOL 80 mg/100 mL
INACTIVE INGREDIENTS: AVENA SATIVA FLOWERING TOP; STEARETH-20 METHACRYLATE; SODIUM CHLORIDE NA-22; WATER; .ALPHA.-(.ALPHA.-AMINOPROPYL)BENZYL ALCOHOL; GLYCERIN; DISTEARYLDIMONIUM CHLORIDE; SHEA BUTTER; PETROLATUM; ISOPROPYL PALMITATE

ACTIVE INGREDIENT

ETYL ALCOHOL 0.80%

PURPOSE

Skin Protectant

Keep out of reach of children. If swallowed get medical help or contact a Poison Control Center immediately.

INDICATION AND USAGE

Relieves dry, itchy skin and provides hydration.

DIRECTIONS

Adults and children over two years of age. Apply up to 3-4 times a day.

Chilldren under two years of age, consult a physician.

WARNING

- For external use only - hands
- Stop use and contact a doctor if condition worsens and does not improve in seven days.
- Avoid contact with eyes. In case of contact with eyes, flush thoroughly with water

INACTIVE INGREDIENTS

WATER

GLYCERIN

DISTEARYLDIMONIUM CHLORIDE

PETROLATUM

ISOPROPYL PALMITATE

AVENA SATIVA (OAT) KERNEL FLOUR

BENZYL ALCOHOL

AVENA SATIVA (OAT) KERNEL OIL

STEARETH-20

AVENA SATIVA (OAT) KERNEL EXTRACT

BUTYROSPERMUM PARKII (SHEA BUTTER)

SODIUM CHLORIDE